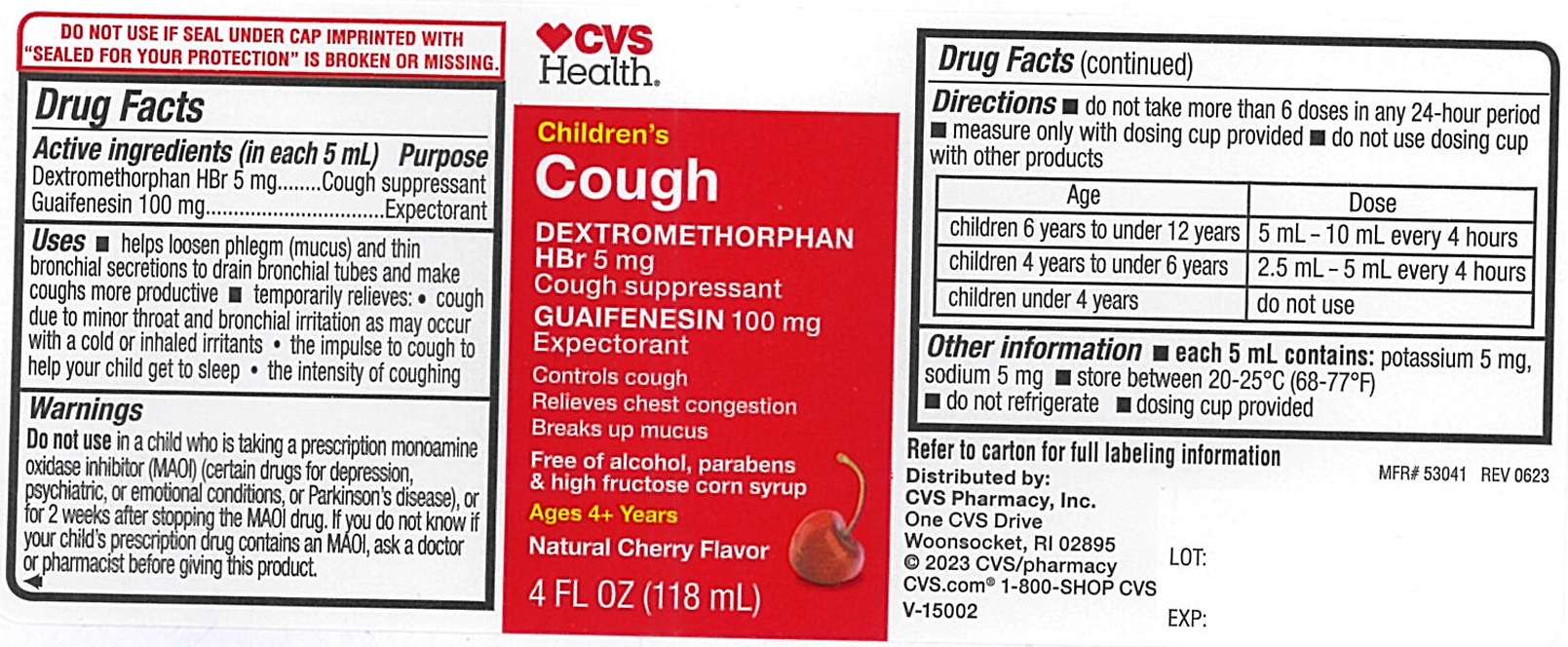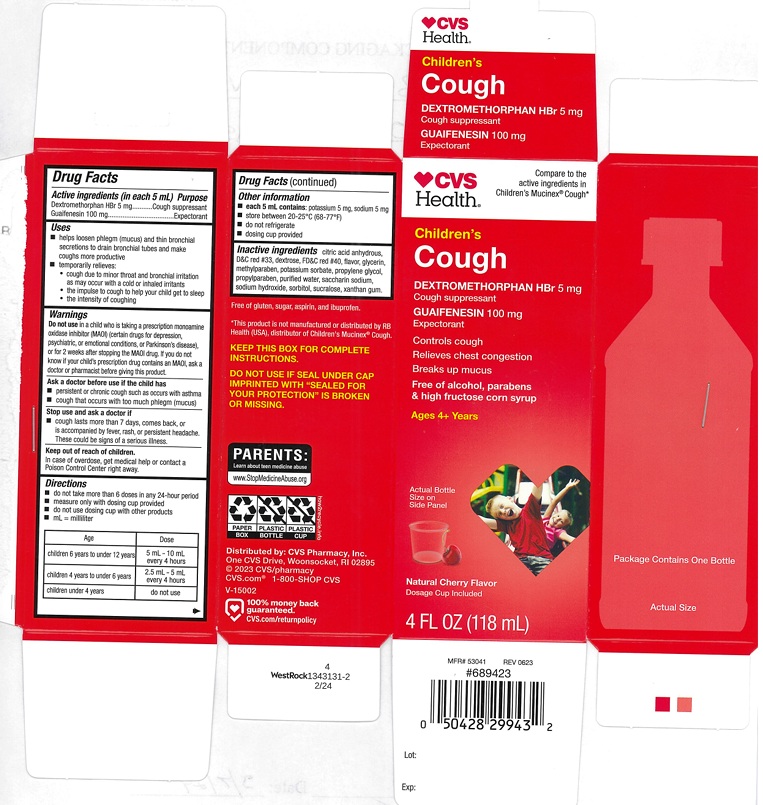 DRUG LABEL: Childrens Mucus and Cough Relief
NDC: 51316-552 | Form: LIQUID
Manufacturer: CVS
Category: otc | Type: Human OTC Drug Label
Date: 20250129

ACTIVE INGREDIENTS: DEXTROMETHORPHAN HYDROBROMIDE 5 mg/5 mL; GUAIFENESIN 100 mg/5 mL
INACTIVE INGREDIENTS: ANHYDROUS CITRIC ACID; DEXTROSE, UNSPECIFIED FORM; D&C RED NO. 33; FD&C RED NO. 40; GLYCERIN; METHYLPARABEN; POTASSIUM SORBATE; PROPYLENE GLYCOL; PROPYLPARABEN; WATER; SACCHARIN SODIUM; SORBITOL; SODIUM HYDROXIDE; SUCRALOSE; XANTHAN GUM

Childrens Mucus and Cough

ACTIVE INGREDIENTS (in each 5 mL)

Dextromethorphan HBr 5 mg
Guaifenesin 100 mg

PURPOSE

Cough suppressant
Expectorant

USES

- helps loosen phlegm (mucus) and thin bronchial secretions to drain bronchial tubes and make coughs more productive
- temporarily relieves:
  - cough due to minor throat and bronchial irritation as may occur with a cold or inhaled irritants
  - the impulse to cough to help your child get to sleep
  - the intensity of coughing

WARNING

.

DO NOT USE

in a child who is taking a prescription monoamine oxidase inhibitor (MAOI) (certain drugs for depression, psychiatric, or emotional conditions, or parkinson's disease), or for 2 weeks after stopping the MAOI drug. If you do not know if your child's prescription drug contains an MAOI, ask a doctor or pharmacist before giving this product.

ASK A DOCTOR BEFORE USE IF THE CHILD HAS

- persistent or chronic cough such as occurs with asthma
- cough that occurs with too much phlegm (mucus)

STOP USE AND ASK A DOCTOR IF

- cough lasts more than 7 days, comes back, or is accompanied by fever, rash, or persistent headache. These could be signs of a serious illness.

KEEP OUT OF REACH OF CHILDREN

In case of overdose, get medical help or contact a Poison Control Center (1-800-222-1222) right away.

DIRECTIONS

- do not take more than 6 doses in any 24-hour period
- measure only with dosing cup provided
- do not use dosing cup with other products
- mL=milliliter

Age | Dose
children 6 years to under 12 years | 5 mL-10 mL every 4 hours
children 4 years to under 6 years | 2.5 mL - 5 mL every 4 hours
children under 4 years | do not use

OTHER INFORMATION

- each 5 mL contains: potassium 5 mg, sodium 5 mg
- store between 20 to 25°C (68 to 77°F)
- do not refrigerate
- dosing cup provided

INACTIVE INGREDIENTS

citric acid anhydrous, dextrose, D&C red#33, FD&C red#40, flavor, glycerin, methylparaben, potassium sorbate, propylene glycol, propyl paraben, purified water, saccharin sodium, sodium hydroxide, sorbitol, sucralose, xanthan gum

PRINCIPAL DISPLAY PANEL

CVS Health

Compare to the active ingredients in Children's Mucinex® Cough*

NDC 51316-552-03

Children's

Cough

Dextromethorphan HBr 5mg

cough Suppressant

Guaifenesin 100 mg

Expectorant

Controls Cough

Relieves Chest Congestion

Breaks up mucus

Free of alcohol, parabens
& high fructose corn syrup

Ages 4+ Years

Natural Cherry Flavor

Dosage Cup Included

4 FL OZ (118mL)